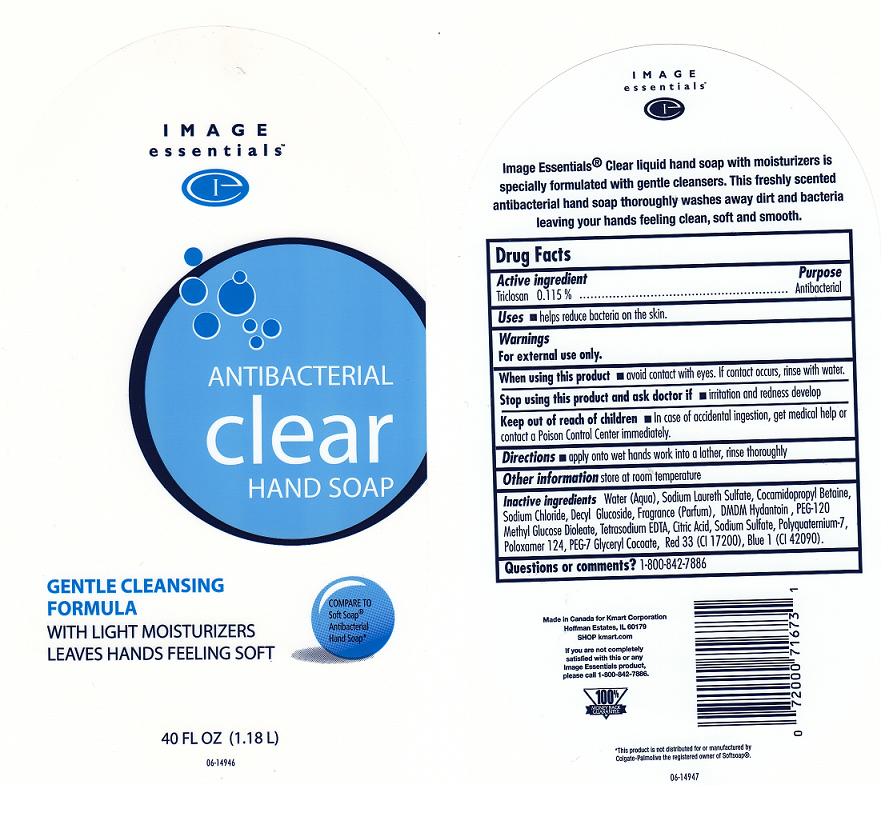 DRUG LABEL: IMAGE ESSENTIALS
NDC: 49738-720 | Form: SOAP
Manufacturer: KMART CORPORATION
Category: otc | Type: HUMAN OTC DRUG LABEL
Date: 20101109

ACTIVE INGREDIENTS: TRICLOSAN 0.115 mL/100 mL
INACTIVE INGREDIENTS: WATER; SODIUM LAURETH SULFATE; SODIUM LAURYL SULFATE; COCAMIDOPROPYL BETAINE; COCO MONOETHANOLAMIDE; SODIUM CHLORIDE; POLYQUATERNIUM-7 (70/30 ACRYLAMIDE/DADMAC; 1600 KD); DMDM HYDANTOIN; EDETATE SODIUM; CITRIC ACID MONOHYDRATE; PEG-120 METHYL GLUCOSE DIOLEATE; FD&C BLUE NO. 1; D&C RED NO. 33

Active Ingredient

Triclosan 0.115%

Purpose

Antibacterial

Warnings

For external use only.

When using this product

- Avoid contact with eyes. If contact occurs, rinse with water.

Stop using this product and ask doctor if

- irritation or redness develops and lasts.

Keep out of reach of children

In case of accidental ingestion, get medical help or contact a Poison Control Center immediately.

Directions

Apply onto wet hands, work into a lather, rinse thoroughly.

Uses

Helps reduce bacteria on the skin

Inactive Ingredients

Water, Sodium Laureth Sulfate, Cocamide MEA, Cocamidopropyl Betaine, Sodium Lauryl Sulfate, Decyl Polyglucose, Sodium Chloride, Fragrance (Parfum), DMDM Hydantoin, PEG-120 Methyl Glucose Dioleate, Citric Acid, Tetrasodium EDTA, Polyquaternium-7, PEG- 7 Glyceryl Cocoate, Red 33 (CI 17200), Blue 1 (CI 42090).

Package Front and Back Labels

IE.jpg